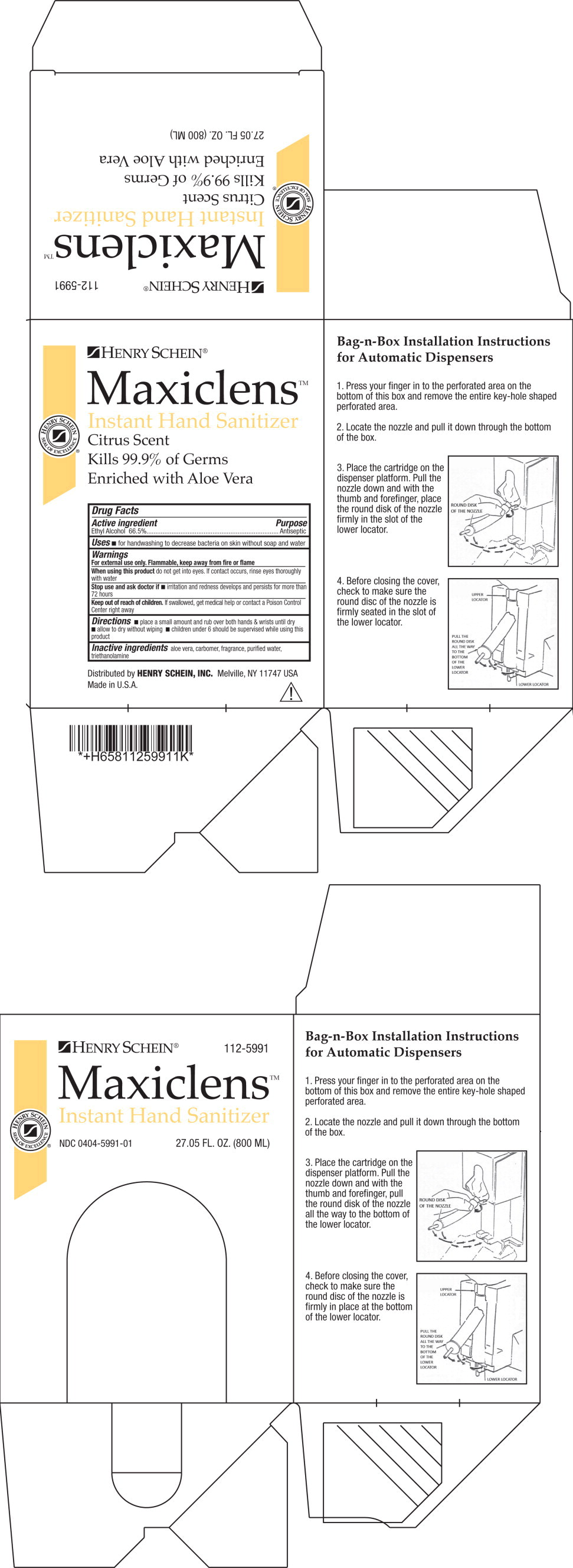 DRUG LABEL: Instant Hand Sanitizer
NDC: 0404-5991 | Form: GEL
Manufacturer: Henry Schein, Inc.
Category: otc | Type: HUMAN OTC DRUG LABEL
Date: 20250110

ACTIVE INGREDIENTS: ALCOHOL 665 mL/1000 mL
INACTIVE INGREDIENTS: ALOE; WATER; TROLAMINE

0404-5991, Maxiclens Instant Hand Sanitizer

Drug Facts

Active Ingredient

Ethyl Alcohol 66.5%

Purpose

Antiseptic

Uses

- for handwashing to decrease bacteria on skin without soap and water

Warnings

For external use only. Flammable, keep away from fire or flame

WHEN USING

When using this productdo not get into eyes. If contact occurs, rinse eyes thoroughly with water

Stop use and ask doctor if

- irritation and redness develops and persists for more than 72 hours

Keep out of reach of children.If swallowed, get medical help or contact a Poison Control Center right away

Directions

- place a small amount and rub over both hands & wrists until dry
- allow to dry without wiping
- children under 6 should be supervised while using this product

Inactive Ingredients

aloe vera, carbomer, fragrance, purified water, triethanolamine

Distributed by HENRY SCHEIN, INC.Melville, NY 11747 USA
Made in U.S.A.

PRINCIPAL DISPLAY PANEL – 27.05 fl. oz. Box Label

Henry Schein

112-5991

Maxiclens

Instant Hand Sanitizer

NDC 0404-5991-01

27.05 FL. OZ. (800 ML)